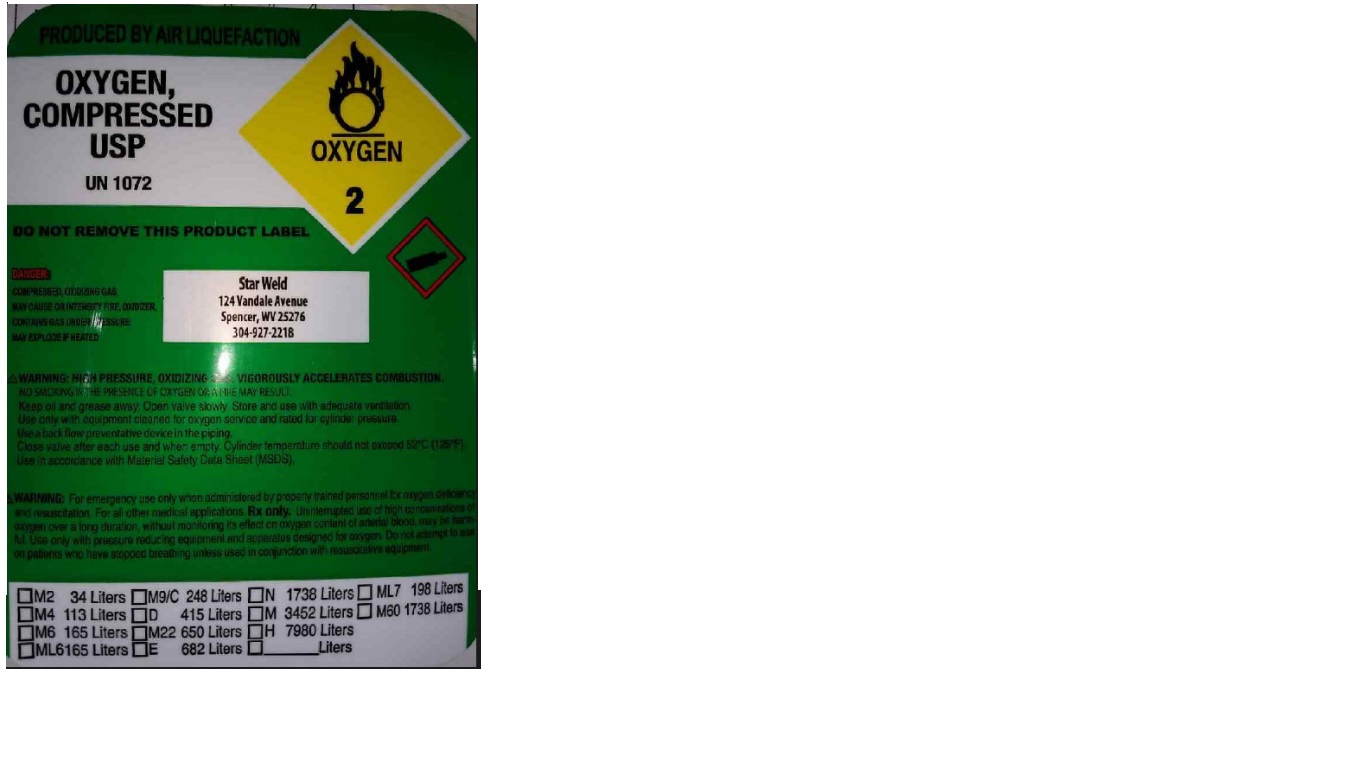 DRUG LABEL: Oxygen
NDC: 51607-001 | Form: GAS
Manufacturer: Star Weld
Category: prescription | Type: HUMAN PRESCRIPTION DRUG LABEL
Date: 20181005

ACTIVE INGREDIENTS: OXYGEN 990 mL/1 L

Oxygen Label

PACKAGE LABEL

PRODUCED BY AIR LIQUEFACTION
OXYGEN, COMPRESSED USP
UN1072
DO NOT REMOVE THIS PRODUCT LABEL
DANGER:
COMPRESSED, OXIDIZING GAS, MAY CUASE OR INTENSIFY FIRE, OXIDIZER. CONTAINS GAS UNDER PRESSURE; MAY EXPLODE IF HEATED.
Star Weld
124 Vandale Avenue
Spencer, WV 25276
304-927-2218
WARNING: HIGH PRESSURE, OXIDIZING GAS. VIGOROUSLY ACCELERATES COMBUSTION.
NO SMOKING IN THE PRESENCE OF OXYGEN OR A FIRE MAY RESULT.
Keep oil and grease away. Open valve slowly. Store and use with adequate ventilation. Use only with equipment cleaned for oxygen service and rated for cylinder pressure. Use a back flow preventive device in the piping. Close valve after each use and when empty. Cylinder temperature should not exceed 52 C (125 F). Use in accordance with Material Safety Data Sheet (MSDS).
WARNING: For emergency use only when administered by properly trained personnel for oxygen deficiency and resuscitation. For all other medical applications, Rx only. Uninterrupted use of high concentrations of oxygen over a long duration, without monitoring its effect on oxygen content of arterial blood, may be harmful. Use only with pressure reducing equipment and apparatus designed for oxygen. Do not attempt to use on patients who have stopped breathing unless used in conjunction with resuscitative equipment.
M2 34 Liters M9/C 248 Liters N 1738 Liters ML7 198 Liters
M4 113 Liters D 415 Liters M 3452 Liters M60 1738 Liters
M6 165 Liters M22 650 Liters H 7980 Liters
ML6165 Liters E 682 Liters Liters